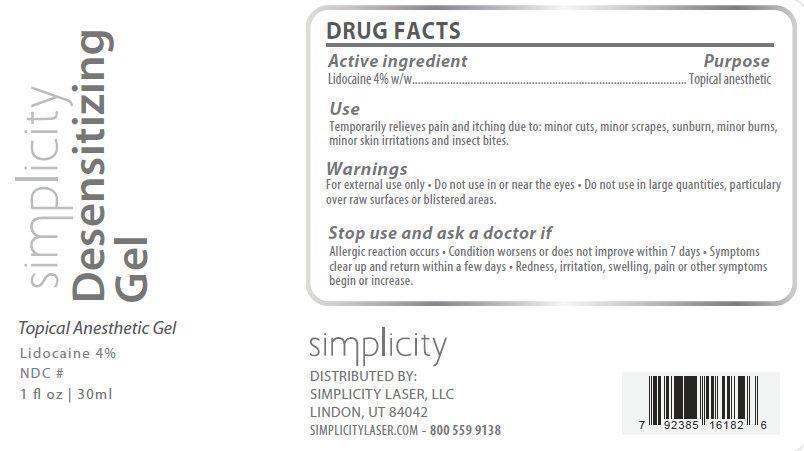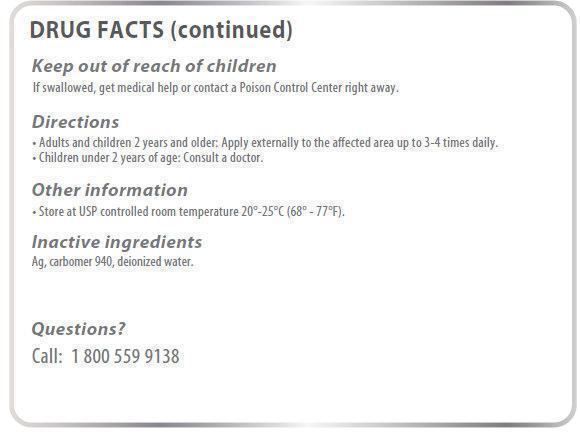 DRUG LABEL: Simplicity Desensitizing
NDC: 69109-004 | Form: GEL
Manufacturer:  Simplicity Laser, LLC
Category: otc | Type: HUMAN OTC DRUG LABEL
Date: 20140715

ACTIVE INGREDIENTS: LIDOCAINE 40 mg/1 mL
INACTIVE INGREDIENTS: CARBOMER HOMOPOLYMER TYPE C; WATER

Simplicity Desensitizing Gel

Active Ingredient:

Lidocaine 4% w/w

Purpose

Topical anesthetic

Use:

temporarily relieves pain and itching due to:

- minor cuts
- minor scrapes
- sunburn
- minor skin irritations
- minor burns
- insect bites

Warnings:

For external use only.

- do not use in or near the eyes
- do not use in large quantities, particularly over raw surfaces or blistered areas

Stop use and ask doctor if

- Allergic reaction occurs
- Condition worsens or does not improve within 7 days
- Symptoms clear up and return within a few days
- Redness, irritation, swelling, pain or other symptoms begin or increase

Keep out of reach of children.

If swallowed, get medical help or contact a Poison Control Center right away.

Directions:

- Adults and children 2 years and older: Apply externally to the affected area up to 3-4 times daily.
- Children under 2 years of age: Consult a doctor.

Other Information

Store at USP controlled room temperature 20-25 deg.C (68-77 deg.F).

Inactive ingredients

Ag,carbomer 940, deionized water